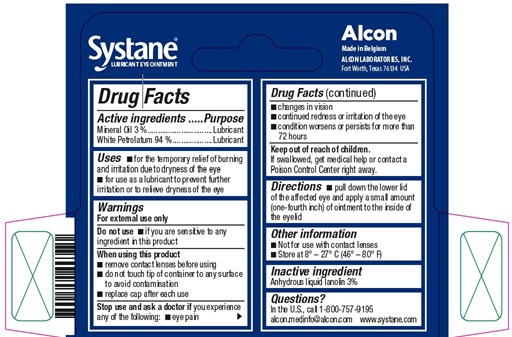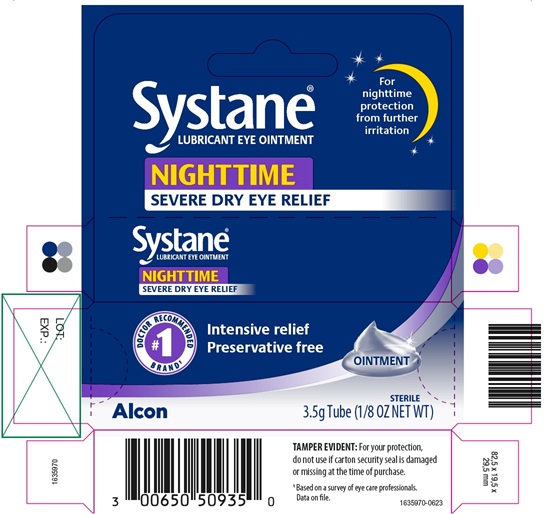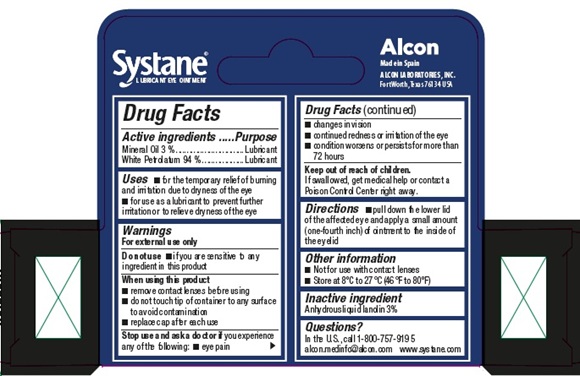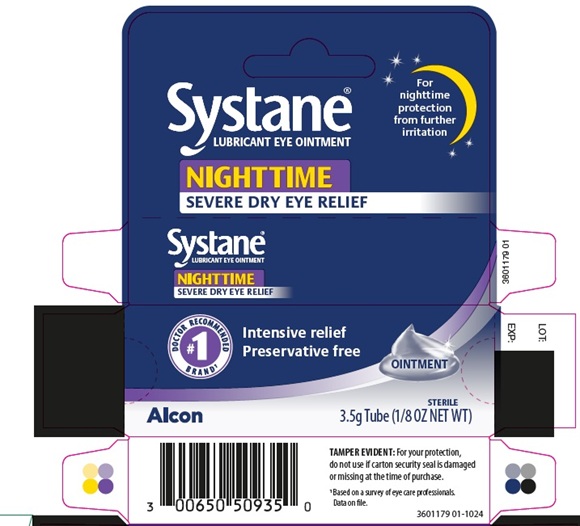 DRUG LABEL: Systane Nighttime
NDC: 0065-0509 | Form: OINTMENT
Manufacturer: Alcon Laboratories, Inc.
Category: otc | Type: HUMAN OTC DRUG LABEL
Date: 20241205

ACTIVE INGREDIENTS: Mineral Oil 30 mg/1 g; Petrolatum 940 mg/1 g
INACTIVE INGREDIENTS: Lanolin

Systane® Nighttime
Drug Facts

Active ingredients | Purpose
Mineral Oil 3% | Lubricant
White Petrolatum 94% | Lubricant

Uses

- for the temporary relief of burning and irritation due to dryness of the eye
- for use as a lubricant to prevent further irritation or to relieve dryness of the eye

Warnings

For external use only
Do not use

- if you are sensitive to any ingredient in this product

When using this product

- remove contact lenses before using
- do not touch tip of container to any surface to avoid contamination
- replace cap after each use

Stop use and ask a doctor if you are experiencing any of the following:

- eye pain
- changes in vision
- continued redness or irritation of the eye
- condition worsens or persist for more than 72 hours

Keep out of reach of children. If swallowed, get medical help or contact a Poison Control Center right away.

Directions

Pull down the lower lid of the affected eye and apply a small amount (one-fourth inch) of ointment to the inside of the eyelid.

Other information

- Not for use with contact lenses
- Store at 8° - 27° C (46° - 80° F)

Inactive ingredient

anhydrous liquid lanolin 3%

QUESTIONS

Questions? In the U.S. call 1-800-757-9195 alcon.medinfo@alcon.com www.systane.com

PRINCIPAL DISPLAY PANEL

Systane®
LUBRICANT EYE OINTMENT
NIGHTTIME
SEVERE DRY EYE RELIEF
For nighttime protection from further irritation
Systane®
LUBRICANT EYE OINTMENT
NIGHTTIME
SEVERE DRY EYE RELIEF
#1 DOCTOR RECOMMENDED BRAND^1
Intensive relief
Preservative free
OINTMENT
Alcon
STERILE
3.5 g Tube (1/8 OZ NET WT)
TAMPER EVIDENT: For your protection,
do not use if carton security seal is damaged
or missing at the time of purchase.
1 Based on a survey of eye care professionals.
Data on file.
1635970-0623
LOT:
EXP.:
Systane®
LUBRICANT EYE OINTMENT
Alcon
Made in Belgium
ALCON LABORATORIES, INC.
Fort Worth, Texas 76134 USA

Systane®
LUBRICANT EYE OINTMENT
NIGHTTIME
SEVERE DRY EYE RELIEF
For nighttime protection from further irritation
Systane®
LUBRICANT EYE OINTMENT
NIGHTTIME
SEVERE DRY EYE RELIEF
#1 DOCTOR RECOMMENDED BRAND^1
Intensive relief
Preservative free
OINTMENT
Alcon
STERILE
3.5 g Tube (1/8 OZ NET WT)
TAMPER EVIDENT: For your protection, do not use if carton security seal is damaged or missing at the time of purchase.
^1 Based on a survey of eye care professionals.
Data on file.
3601179 01-1024
Systane®
LUBRICANT EYE OINTMENT
Alcon
Made in Spain
ALCON LABORATORIES, INC.
Fort Worth, Texas 76134 USA